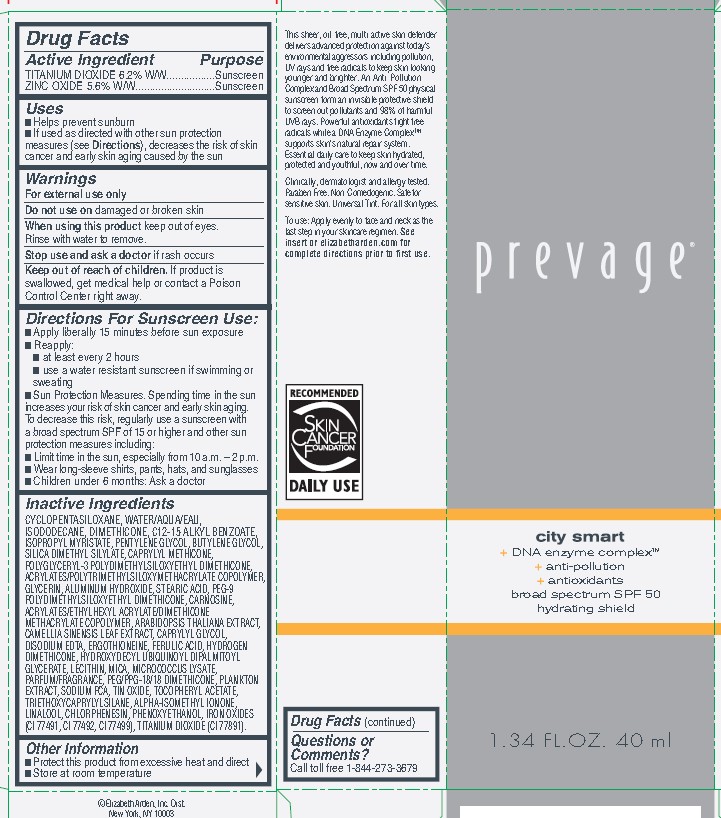 DRUG LABEL: PREVAGE CITY SMART
NDC: 10967-670 | Form: EMULSION
Manufacturer: REVLON
Category: otc | Type: HUMAN OTC DRUG LABEL
Date: 20240112

ACTIVE INGREDIENTS: ZINC OXIDE 5.6 mg/1 g; TITANIUM DIOXIDE 6.2 mg/1 g
INACTIVE INGREDIENTS: ARABIDOPSIS THALIANA WHOLE; PEG-9 POLYDIMETHYLSILOXYETHYL DIMETHICONE; PHENOXYETHANOL; LINALOOL, (+/-)-; DIMETHICONE; ALKYL (C12-15) BENZOATE; CAPRYLYL TRISILOXANE; ISOMETHYL-.ALPHA.-IONONE; FERRIC OXIDE RED; LECITHIN, SOYBEAN; MICA; PEG/PPG-18/18 DIMETHICONE; SODIUM PYRROLIDONE CARBOXYLATE; WATER; HYDROGEN DIMETHICONE (20 CST); HYDROXYDECYL UBIQUINOYL DIPALMITOYL GLYCERATE; CYCLOMETHICONE 5; PENTYLENE GLYCOL; BUTYLENE GLYCOL; POLYGLYCERYL-3 POLYDIMETHYLSILOXYETHYL DIMETHICONE (4000 MPA.S); GREEN TEA LEAF; CAPRYLYL GLYCOL; EDETATE DISODIUM ANHYDROUS; ERGOTHIONEINE; CARNOSINE; ISOPROPYL MYRISTATE; SILICA DIMETHYL SILYLATE; FERULIC ACID; STANNIC OXIDE; .ALPHA.-TOCOPHEROL ACETATE; GLYCERIN; ALUMINUM HYDROXIDE; CHLORPHENESIN; FERRIC OXIDE YELLOW; FERROSOFERRIC OXIDE; ISODODECANE; STEARIC ACID

ELIZABETH ARDEN PREVAGE CITY SMART BROAD SPECTRUM HYDRATING SHIELD

ACTIVE INGREDIENTS

TITANIUM DIOXIDE 6.2% W/W.................Sunscreen
ZINC OXIDE 5.6% W/W ............................Sunscreen

INACTIVE INGREDIENTS

CYCLOPENTASILOXANE, WATER/AQUA/EAU, ISODODECANE, DIMETHICONE, C12-15 ALKYL BENZOATE, ISOPROPYL MYRISTATE, PENTYLENE GLYCOL, BUTYLENE GLYCOL, SILICA DIMETHYL SILYLATE, CAPRYLYL METHICONE,
POLYGLYCERYL-3 POLYDIMETHYLSILOXYETHYL DIMETHICONE, ACRYLATES/POLYTRIMETHYLSILOXYMETHACRYLATE COPOLYMER, GLYCERIN, ALUMINUM HYDROXIDE, STEARIC ACID, PEG-9 POLYDIMETHYLSILOXYETHYL DIMETHICONE, CARNOSINE, ACRYLATES/ETHYLHEXYL ACRYLATE/DIMETHICONE METHACRYLATE COPOLYMER, ARABIDOPSIS THALIANA EXTRACT, CAMELLIA SINENSIS LEAF EXTRACT, CAPRYLYL GLYCOL, DISODIUM EDTA, ERGOTHIONEINE, FERULIC ACID, HYDROGEN DIMETHICONE, HYDROXYDECYL UBIQUINOYL DIPALMITOYL GLYCERATE, LECITHIN, MICA, MICROCOCCUS LYSATE, PARFUM/FRAGRANCE, PEG/PPG-18/18 DIMETHICONE, PLANKTON EXTRACT, SODIUM PCA, TIN OXIDE, TOCOPHERYL ACETATE, TRIETHOXYCAPRYLYLSILANE, ALPHA-ISOMETHYL IONONE, LINALOOL, CHLORPHENESIN, PHENOXYETHANOL, IRON OXIDES (CI 77491, CI 77492, CI 77499), TITANIUM DIOXIDE (CI 77891).

USES

■ Helps prevent sunburn
■ If used as directed with other sun protection measures (see Directions), decreases the risk of skin cancer and early skin aging caused by the sun

WARNINGS

For external use only
Do not use on damaged or broken skin
When using this product keep out of eyes. Rinse with water to remove.
Stop use and ask a doctor if rash occurs
Keep out of reach of children. If product is swallowed, get medical help or contact a Poison Control Center right away.

DIRECTIONS FOR SUNSCREEN USE

■ Apply liberally 15 minutes before sun exposure
■ Reapply:

- at least every 2 hours
- use a water resistant sunscreen if swimming or sweating

■ Sun Protection Measures. Spending time in the sun increases your risk of skin cancer and early skin aging. To decrease this risk, regularly use a sunscreen with a broad spectrum SPF of 15 or higher and other sun protection measures including:
■ Limit time in the sun, especially from 10 a.m. – 2 p.m.
■ Wear long-sleeve shirts, pants, hats, and sunglasses
■ Children under 6 months: Ask a doctor

OTHER INFORMATION

■ Protect this product from excessive heat and direct
■ Store at room temperature

DOSAGE AND ADMINISTRATION

As needed

INDICATIONS AND USAGE

- Helps prevent sunburn

Keep out of reach of children. If product is swallowed, get medical help or contact a Poison Control Center right away.

PURPOSE

Sunscreen